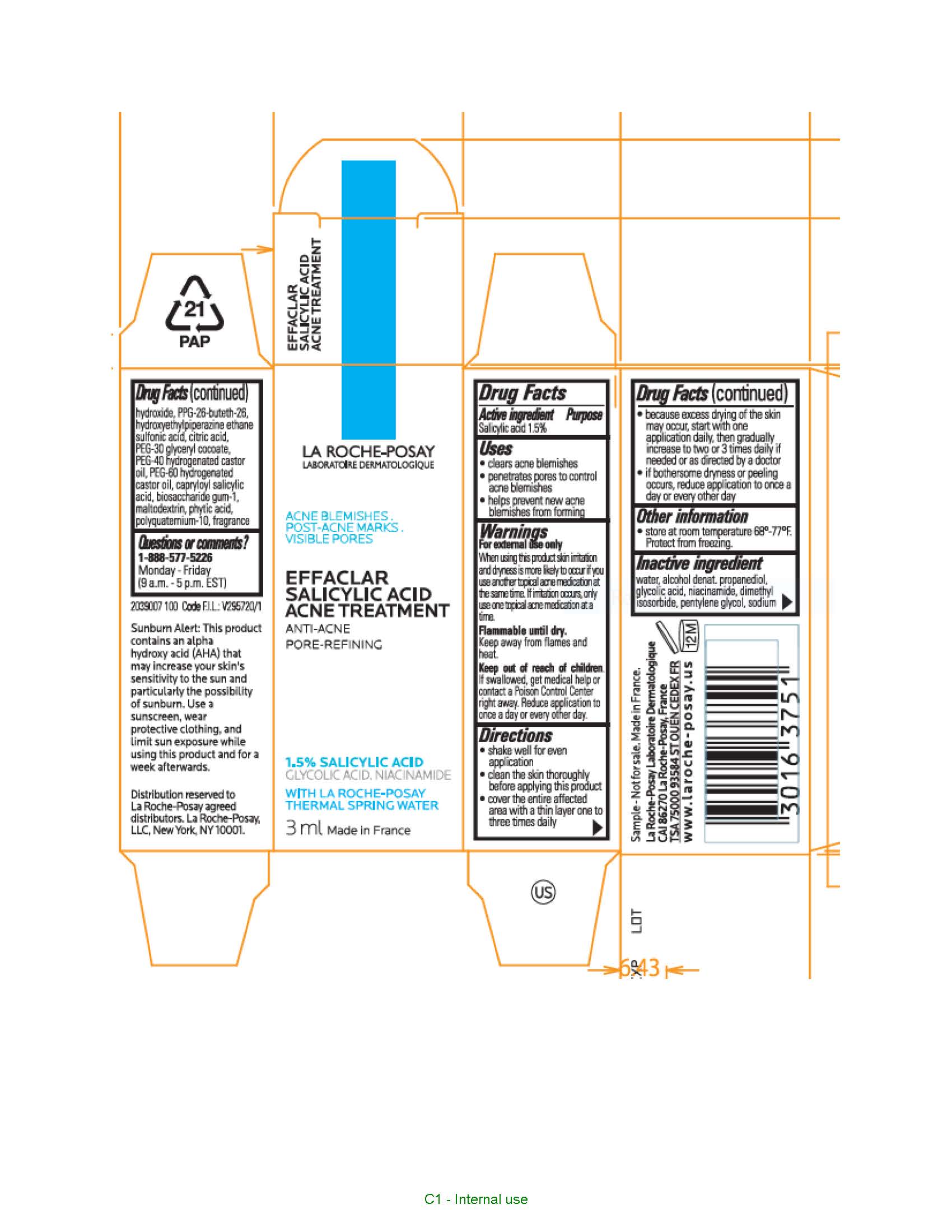 DRUG LABEL: La Roche Posay Laboratoire Dermatologique Effaclar Pore Refining Acne Treatment
NDC: 49967-529 | Form: LIQUID
Manufacturer: L'Oreal USA Products Inc
Category: otc | Type: HUMAN OTC DRUG LABEL
Date: 20231213

ACTIVE INGREDIENTS: SALICYLIC ACID 15 mg/1 mL
INACTIVE INGREDIENTS: WATER; ALCOHOL; PROPANEDIOL; GLYCOLIC ACID; NIACINAMIDE; DIMETHYL ISOSORBIDE; PENTYLENE GLYCOL; SODIUM HYDROXIDE; PPG-26-BUTETH-26; HYDROXYETHYLPIPERAZINE ETHANE SULFONIC ACID; CITRIC ACID MONOHYDRATE; PEG-30 GLYCERYL COCOATE; POLYOXYL 40 HYDROGENATED CASTOR OIL; PEG-60 HYDROGENATED CASTOR OIL; CAPRYLOYL SALICYLIC ACID; BIOSACCHARIDE GUM-1; MALTODEXTRIN; FYTIC ACID; POLYQUATERNIUM-10 (10000 MPA.S AT 2%)

Drug Facts

Active ingredient

Salicylic acid 1.5%

Purpose

Acne treatment

Uses

- clears acne blemishes
- penetrates pores to control acne blemishes
- helps prevent new acne blemishes from forming

Warnings

For external use only

Keep out of reach of children.

If swallowed, get medical help or contact a Poison Control Center right away.

Directions

- clean the skin thoroughly before applying this product
- cover the entire affected area with a thin layer one to three times daily
- because excessive drying of the skin may occur, start with one application daily, then gradually increase to two or three times daily if needed or as directed by a doctor
- if bothersome dryness or peeling occurs, reduce application to once a day or every other day
- children under 12 years of age: ask a doctor

Inactive ingredients

water, alcohol denat., propanediol, glycolic acid, niacinamide, dimethyl isosorbide, pentylene glycol, sodium hydroxide, capitolize-26-buteth-26, PPG-26-buteth-26, hydroxyethylpiperazine ethane sulfonic acid, citric acid, PEG-30 glyceryl cocoate, PEG-40 hydrogenated castor oil, PEG-60 hydrogenated castor oil, capryloyl salicylic acid, biosaccharide gum-1, maltodextrin, phytic acid, polyquaternium-10, fragrance

Questions or comments?

1-888-LRP LABO

1-888-577-5226

Monday - Friday (9 a.m. - 5 p.m. EST)